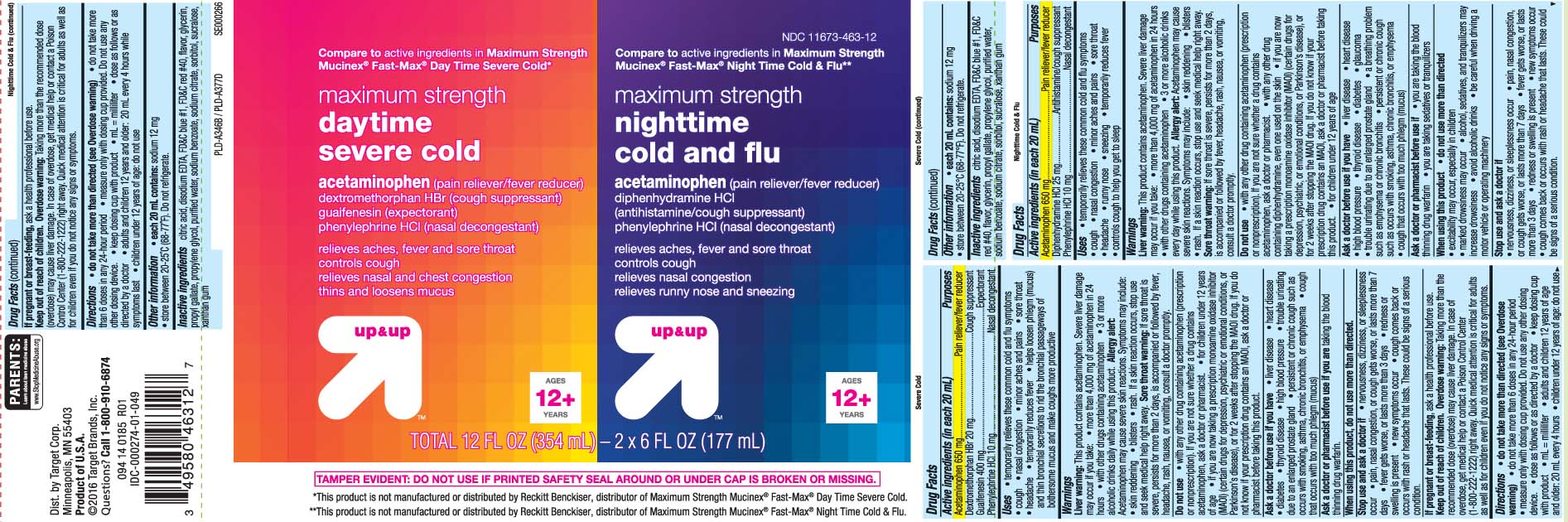 DRUG LABEL: DayTime Mucus Relief Severe Cold and Nighttime Cold and Flu
NDC: 11673-463 | Form: KIT | Route: ORAL
Manufacturer: TARGET Corporation
Category: otc | Type: HUMAN OTC DRUG LABEL
Date: 20241112

ACTIVE INGREDIENTS: DEXTROMETHORPHAN HYDROBROMIDE 20 mg/20 mL; GUAIFENESIN 400 mg/20 mL; PHENYLEPHRINE HYDROCHLORIDE 10 mg/20 mL; ACETAMINOPHEN 650 mg/20 mL; ACETAMINOPHEN 650 mg/20 mL; DIPHENHYDRAMINE HYDROCHLORIDE 25 mg/20 mL; PHENYLEPHRINE HYDROCHLORIDE 10 mg/20 mL
INACTIVE INGREDIENTS: FD&C BLUE NO. 1; PROPYLENE GLYCOL; WATER; FD&C RED NO. 40; ANHYDROUS CITRIC ACID; EDETATE CALCIUM DISODIUM; SODIUM BENZOATE; TRISODIUM CITRATE DIHYDRATE; GLYCERIN; PROPYL GALLATE; SORBITOL; SUCRALOSE; XANTHAN GUM; GLYCERIN; PROPYLENE GLYCOL; WATER; SORBITOL; ANHYDROUS CITRIC ACID; FD&C BLUE NO. 1; FD&C RED NO. 40; SODIUM BENZOATE; SODIUM CITRATE; SUCRALOSE; PROPYL GALLATE; XANTHAN GUM; EDETATE CALCIUM DISODIUM

DRUG FACTS

Active ingredients for Nighttime (in each 20 mL)

Acetaminophen 650 mg

Diphenhydramine HCI 25 mg

Phenylephrine HCI 10 mg

Active ingredients for Daytime (in each 20 mL)

Acetaminophen 650 mg

Dextromethorphan HBr 20 mg

Guaifeenesin 400 mg

Phenylephrine HCl 10 mg

Purpose for Nighttime

Pain reliever/fever reducer

Antihistamine/cough suppressant

Nasal decongestant

Purpose for Daytime

Pain reliever / fever reducer

Cough suppressant

Expectorant

Nasal decongestant

Uses

Nighttime

- temporarily relieves these common cold and flu symptoms
- cough
- nasal congestion
- minor aches and pains
- sore throat
- headache
- runny nose
- sneezing
- temporarily reduces fever
- controls cough to help you get to sleep

Daytime

- temporarily relieves these common cold and flu symptoms
- cough
- nasal congestion
- minor aches and pains
- sore throat
- headache
- temporarily reduces fever
- helps loosen phlegm (mucus) and thin bronchial secretions to rid the bronchial passageways of bothersome mucus and make cough more productive

Warnings

NIGHTTIME and DAYTIME

Liver warning: This product contain acetaminophen. Severe liver damage may occur if you take

- more than 4,000 mg of acetaminophen in 24 hours
- with other drugs containing acetaminophen
- 3 or more alcoholic drinks every day while using this product.

Allergy alert: Acetaminophen may cause severe skin reactions. Symptoms may include:

- skin reddening
- blisters
- rash.

If a skin reaction occurs, stop use and seek medical help right away.

Sore throat warning: If sore throat is severe, persists for more than 2 days, is accompanied or followed by fever, headache, rash, nausea, or vomiting, consult a doctor promptly.

Do not use

Nighttime

- with any drug containing acetaminophen (prescription or nonprescription) . If you are not sure whether a drug contains acetaminophen, ask a doctor or pharmacist.
- with any other drug containing diphenhydramine, even one used on the skin
- if you are now taking a prescription monoamine oxidase inhibitor (MAOI) (certain drugs for depression, psychiatric or emotional conditions, or Parkinson’s disease), or for 2 weeks after stopping the MAOI drug. If you do not know if your prescription drug contains an MAOI, ask a doctor or pharmacist before taking this product
- for children under 12 years of age

Daytime

- with any other drug containing acetaminophen (prescription or non prescription). If you are not sure whether a drug contains acetaminophen, ask a doctor or pharmacist.
- for children under 12 years of age
- if you are now taking a prescription monoamine oxidase inhibitor (MAOI)(certain drugs for depression,psychiatic or emotional conditions, or Parkinson's disease), or for 2 weeks after stopping the MAOI drug. If you do not know if your prescription drug contains an MAOI, ask a doctor or pharmacist before taking this product.

Ask a doctor before use if you have

Nighttime

- liver disease
- heart disease
- high blood pressure
- thyroid disease
- diabetes
- glaucoma
- trouble urinating due to an enlarged prostate gland
- a breathing problem such as emphysema or chronic bronchitis
- persistent or chronic cough such as occurs with smoking, asthma, chronic bronchitis, or emphysema
- cough that occurs with too much phlegm (mucus)

Daytime

- liver disease
- heart disease
- high blood pressure
- thyroid disease
- diabetes
- trouble urinating due to an enlarged gland
- persistent or chronic cough such as occurs with smoking, asthma, chronic bronchitis, or emphtsema
- cough that occurs with too much phlegm (mucus)

Ask a doctor or pharmacist before use if you are

Nighttime

- you are taking the blood thinning drug warfarin
- you are taking sedative or tranquilizers

Daytime

- taking the blood thinning drug warfarin

When using these products

Nighttime

- do not use more than directed
- excitability may occur, especially in children
- marked drowsiness may occur
- alcohol, sedatives and tranquilizers may increase drowsiness
- avoid alcoholic drinks
- be careful when driving a motor vehicile or operating machinery

Daytime

- do not use more than directed

Stop use and ask a doctor if

Nighttime

- nervousness, dizziness, or sleeplessness occur
- pain, nasal congestion, or cough gets worse, or lasts more than 7 days
- fever gets worse, or last more than 3 days
- redness or swelling is present
- new symptoms occur
- cough comes back or occurs with rash or headache that lasts. These could be a signs of a serious condition

Daytime

- nervousness, dizziness or sleeplessness occur
- pain, nasal congestion, or cough gets worse, or lasts more than 7 days
- fever gets worse, or lasts more than 3 days
- redness or swelling is present
- new symptoms occur
- cough comes back or occurs with rash or headache that lasts. These could be signs of a serious condition.

If pregnant or breast-feeding,

Nighttime and DayTime

ask a health professional before use.

Keep out of reach of children.

Nighttime and DayTime

Overdose warning: Taking more than the recommended dose (overdose) may cause liver damage. In case of overdose, get medical help or contact a Poison Control Center (1-800-222-1222) right away. Quick medical attention is critical for adults as well as for children even if you do not notice any signs or symptoms.

Directions

Nighttime

- do not take more than directed (see overdose warning)
- do not take more than 6 doses in any 24-hour period
- measure only with dosing cup provided. Do not use any other dosing device
- keep dosing cup with product
- mL = mililiter
- dose as follows or as directed by a doctor
- adults and children 12 years and older: 20 mL every 4 hours while symptoms last
- children under 12 years of age: do not use

Daytime

- do not take more than directed (see Overdose warning)
- do not take more than 6 doses in any 24-hours period
- measure only with dosing cup provided. Do not use any other dosing device.
- dose as follows or as directed by a doctor
- keep dosing cup with product
- mL = milliliter
- adults and children 12 years of age and older: 20 mL every 4 hours
- children under 12 years of age: do not use

Other information

Nighttime

- each 20 mL contains: sodium 12 mg
- store between 20-25ºC (68-77ºF). Do not refrigerate.

Daytime

- each 20 mL contains: 12 mg
- store between 20-25ºC (68-77ºF). Do not refrigerate.

Inactive ingredients

Nighttime

citric acid, disodium EDTA, FD&C Blue #1, FD&C red #40, Flavor, glycerin, propyl gallate, propylene glycol, purified water, sodium benzoate, sodium citrate, sorbitol, sucralose, xanthan gum

Daytime

citric acid, disodium EDTA, FD&C blue #1, FD&C red #40, flavor, glycerin, propyl gallate, propylene glycol, purified water, sodium benzoate, sodium citrate, sorbitol, sucralose, xanthan gum

Principal Display Panel

NIGHTTIME

Compare to active ingredients in Maximum Strength Mucinex®Fast-Max® Night Time Cold & Flu**

maximum strength

nighttime

Cold & Flu

acetaminophen (pain reliever / fever reducer)

diphenhydramine HCI (antihistamine / cough suppressant)

phenylephrine HCI (nasal decongestant)

Relieves aches, fever, sore throat

controls cough

relieves nasal congestion

relieves runny nose and sneezing

AGES 12 + YEARS

DAYTIME

Compare to active ingredients in Maximum Strength Mucinex® Fast-Max® Day Time Severe Cold*

maximum strength

daytime

Severe Cold

acetaminophen (pain reliever / fever reducer)

dextromethorphan HBr (cough suppressant)

guaifenesin (expectorant)

phenylephrine HCI (nasal decongestant)

Relieves aches, fever & sore throat

Controls Cough

relieves nasal and chest congestion

thins and loosens mucus

AGES 12 + YEARS

TAMPER EVIDENT: DO NOT USE IF PRINTED SAFETY SEAL AROUND OR UNDER CAP IS BROKEN OR MISSING.

*This prodect is not manufactured or distributed by Recitt Benckiser, distributor of Maximum Strength Mucinex® Fast-Max® Day Time Severe Cold.

**This product is not manufactured or distributed by Reckitt Benckiser, distributor of Maximum Strength Mucinex® FAST-MAX® Night Time Cold & Flu.

Dist. by Target Corp.

Minneapolis, MN 55403

Product of U.S.A.

©2016 Target Brands, Inc.

Questions? Call 1-800-910-6874

Product Label

TARGET Maximum Strength Nighttime cold and flu Maximum Strength Daytime Severe Cold